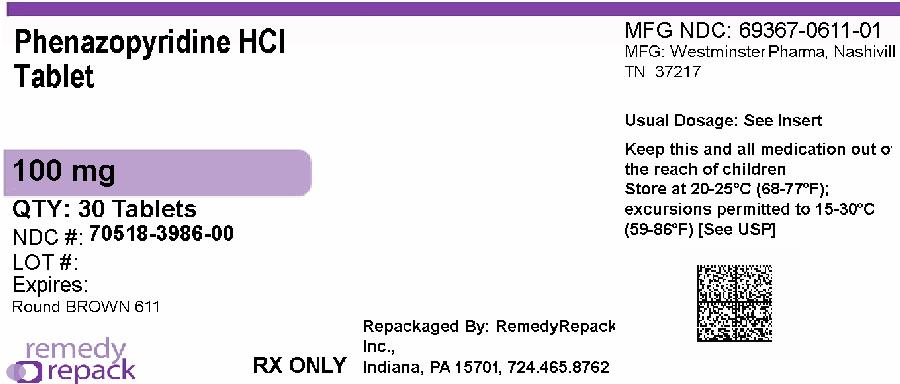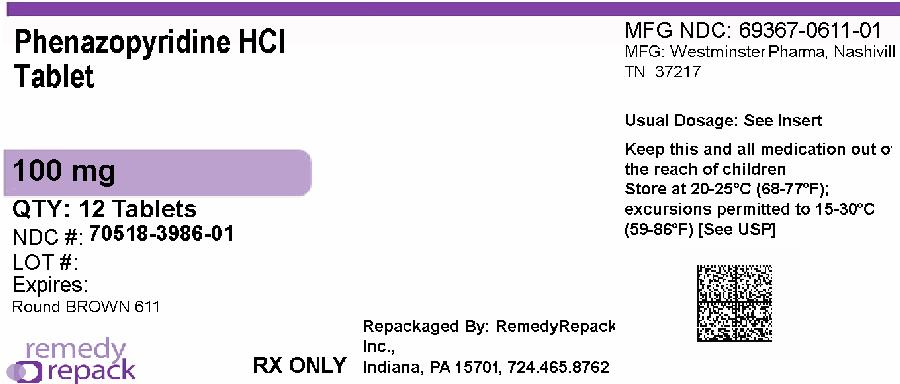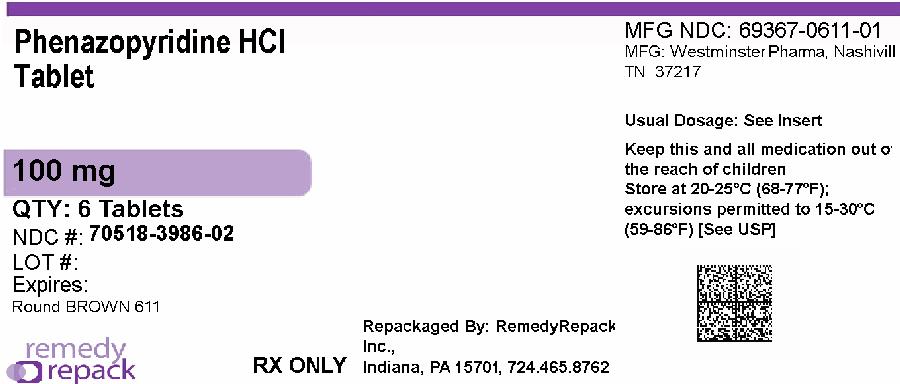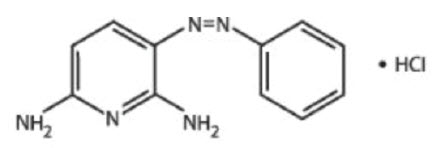 DRUG LABEL: Phenazopyridine Hydrochloride
NDC: 70518-3986 | Form: TABLET
Manufacturer: REMEDYREPACK INC.
Category: prescription | Type: HUMAN PRESCRIPTION DRUG LABEL
Date: 20260218

ACTIVE INGREDIENTS: PHENAZOPYRIDINE HYDROCHLORIDE 100 mg/1 1
INACTIVE INGREDIENTS: CROSCARMELLOSE SODIUM; D&C YELLOW NO. 10; FD&C RED NO. 40; FD&C BLUE NO. 1; FD&C YELLOW NO. 6; MICROCRYSTALLINE CELLULOSE; MAGNESIUM STEARATE; POVIDONE, UNSPECIFIED; POLYVINYL ALCOHOL, UNSPECIFIED; POLYETHYLENE GLYCOL, UNSPECIFIED; SILICON DIOXIDE; TALC; TITANIUM DIOXIDE; STARCH, CORN

PHENAZOPYRIDINE HYDROCHLORIDE
TABLETS, USP

Rx only

Phenazopyridine Hydrochloride – Westminster Pharmaceuticals, LLC
Prescription Medication

Disclaimer:This drug has not been found by FDA to be safe and effective, and this labeling has not been approved by FDA.

Rx Only

DESCRIPTION

Phenazopyridine Hydrochloride is a reddish-brown, odorless, slightly bitter, crystalline powder. It has a specific local analgesic effect in the urinary tract, promptly relieving burning and pain.

Following is the structural formula:

Phenazopyridine Hydrochloride oral tablets contain the following inactive ingredients: Croscarmellose Sodium, D&C Yellow #10 Aluminum Lake, FD&C Blue #1 Aluminum Lake, FD&C Red #40 Aluminum Lake, FD&C Yellow #6 Aluminum Lake, Magnesium Stearate, Microcrystalline Cellulose, Polyethylene Glycol, Polyvinyl Alcohol, Povidone, Pregelatinized Starch, Talc, and Titanium Dioxide.

CLINICAL PHARMACOLOGY

Phenazopyridine hydrochloride is excreted in the urine where it exerts a topical analgesic effect on the mucosa of the urinary tract. This action helps to relieve pain, burning, urgency and frequency. The precise mechanism of action is unknown.

PHARMACOKINETICS

The pharmacokinetic properties of Phenazopyridine hydrochloride have not been determined. Phenazopyridine Hydrochloride and its metabolites are rapidly excreted by the kidneys. In a small number of healthy subjects, 90% of a 600 mg/day oral dose of Phenazopyridine hydrochloride was eliminated in the urine in 24 hours, 41% as unchanged drug and 49% as metabolites.

INDICATIONS AND USAGE

Phenazopyridine Hydrochloride is indicated for the symptomatic relief of pain, burning, urgency frequency, and other discomforts arising from irritation of the mucosa of the lower urinary tract caused by infection, trauma, surgery, endoscopic procedures, or the passage of sounds or catheters.

The use of Phenazopyridine Hydrochloride for relief of symptoms should not delay definitive diagnosis and treatment of causative conditions. The drug should be used for symptomatic relief of pain and not as a substitute for specific surgery or antimicrobial therapy.

Phenazopyridine Hydrochloride is compatible with antimicrobial therapy and can help relieve pain and discomfort during the interval before antimicrobial therapy controls the infection.

Treatment of a urinary tract infection with Phenazopyridine Hydrochloride should not exceed 2 days. There is no evidence that the combined administration of Phenazopyridine Hydrochloride and an antimicrobial provides greater benefit than administration of the antimicrobial alone after 2 days. (See Dosage and Administration.)

CONTRAINDICATIONS

Phenazopyridine Hydrochloride should not be used in patients who are hypersensitive to the drug or its ingredients. Phenazopyridine Hydrochloride is contraindicated in patients with renal insufficiency, severe liver disease, severe hepatitis or pyelonephritis of pregnancy. It should be used cautiously in the presence of GI disturbances.

WARNINGS

Phenazopyridine Hydrochloride is reasonably anticipated to be a human carcinogen based on sufficient evidence of carcinogenicity in experimental animals (IARC 1980, 1982, 1987, NCI 1978). When administered in the diet, Phenazopyridine hydrochloride increased the incidences of hepatocellular adenomas and carcinomas in female mice and adenomas and adenocarcinomas of the colon and rectum in rats of both sexes. There is inadequate evidence for the carcinogenicity of Phenazopyridine hydrochloride in humans (TARC 1987). In one limited epidemiological study, no significant excess of any cancer was observed among 2,214 patients who received Phenazopyridine hydrochloride and were followed for a minimum of 3 years.

PRECAUTIONS

General

The patient should be advised that Phenazopyridine Hydrochloride produces an orange to red color in the urine and feces, and may cause staining. Phenazopyridine Hydrochloride may cause discoloration of body fluids and staining of contact lenses has been reported. A yellowish color of the skin or sclera may indicate accumulation of Phenazopyridine Hydrochloride resulting from impaired renal function and necessitates discontinuance of the drug. It should be noted that a decline in renal function is common in elderly patients. Phenazopyridine Hydrochloride may mask pathological conditions and interfere with laboratory test values using colorimetric, spectrophotometric or fluorometric analysis methods.

Cautious use in patients with G-6-PD deficiency is advised since these patients are susceptible to oxidative hemolysis and may have greater potential to develop hemolytic anemia.

Information for Patients

The patient should be advised to take Phenazopyridine Hydrochloride with or following food or after eating a snack to reduce stomach upset.

The patients should be aware that Phenazopyridine Hydrochloride causes a reddish orange discoloration of the urine and feces, and may stain clothing. Phenazopyridine Hydrochloride may cause discoloration of body fluids and staining of contact lenses has been reported. There have been reports of teeth discoloration when the product has been broken or held in the mouth prior to swallowing.

Patients should be instructed to take Phenazopyridine Hydrochloride for only 2 days if an antibacterial agent is administered concurrently for the treatment of a urinary tract infection.

If symptoms persist beyond those 2 days, the patient should be instructed to contact his or her physician.

Repackaged By / Distributed By: RemedyRepack Inc.

625 Kolter Drive, Indiana, PA 15701

(724) 465-8762

Laboratory Tests

Phenazopyridine Hydrochloride may interfere with laboratory test values using colorimetric, photometric or fluorometric analysis methods.

Altered urine laboratory test values may include ketone (sodium nitroprusside) bilirubin (foam test, talc-disk-Fouchet-spot test, Franklin's tablet-Fouchet test, p-nitrobenzene diazonium p-toluene sulfonate reagent), diacetic acid (Gerhardt ferric chloride test), free hydrochloric acid, glucose (glucose oxidase tests), 17-hydroxycorticosteroids (modified Glenn-Nelson), 17-ketosteroids (Holtorff Koch modification of Zimmerman), porphyrins, albumin (discolors bromophenol blue test areas of commercial reagent strips, nitric acid ring test), phenolsulfophthalein, urobilinogen (color interference with Ehrlich's reagent), and urinalysis (spectrophotometric or color-based tests). Phenazopyridine Hydrochloride also imparts an orange-red color to stools which may interfere with color tests.

Drug Interactions

The interaction of Phenazopyridine Hydrochloride with other drugs has not been studied in a systematic manner. However, the medical literature to date suggests that no significant interactions have been reported.

Carcinogenesis, Mutagenesis, Impairment of Fertility

Long-term administration of Phenazopyridine Hydrochloride has been associated with tumors of the large intestine in rats and of the liver in mice. Available epidemiological data are insufficient to evaluate the carcinogenicity of Phenazopyridine Hydrochloride in humans. In vitro studies indicate that Phenazopyridine Hydrochloride in the presence of metabolic activation is mutagenic in bacteria and mutagenic and clastogenic in mammalian cells.

Pregnancy Category B

Reproductive studies with Phenazopyridine Hydrochloride (in combination with sulfacytine) in rats given up to 110 mg/kg/day and in rabbits given up to 39 mg/kg/day during organogenesis revealed no evidence of harm to offspring.

One prospective study in humans demonstrated that Phenazopyridine Hydrochloride traverses the placenta into the fetal compartment. There are no adequate and well-controlled studies in pregnant women. Therefore, Phenazopyridine Hydrochloride should be used in pregnant women only if the benefit clearly outweighs the risk.

Nursing Mothers

It is not known whether Phenazopyridine Hydrochloride or its metabolites are excreted in human milk. Because many drugs are excreted in human milk, a decision should be made to discontinue nursing or to discontinue the drug, taking into account the importance of drug therapy to the mother.

Children

Adequate and well-controlled studies have not been performed in the pediatric population. No pediatric-specific problems have been documented.

DOSAGE AND ADMINISTRATION

100 mg Tablets: Average adult dosage is two tablets 3 times a day after meals.
200 mg Tablets: Average adult dosage is one tablet 3 times a day after meals.

When used concomitantly with an antibacterial agent for the treatment of a urinary tract infection, the administration of Phenazopyridine Hydrochloride should not exceed 2 days.

ADVERSE REACTIONS

The following adverse events have been reported:

CNS: headache.

Gastrointestinal: nausea, vomiting and diarrhea.

Dermatologic and Hypersensitivity: rash, pruritus, discoloration, anaphylactoid-like reaction and hypersensitivity hepatitis.

Hematologic: methemoglobinemia, hemolytic anemia, potential hemolytic agent in G-6-PD deficiency, sulfhemoglobinemia.

Other: visual disturbances, renal and hepatic toxicity usually associated with overdose, renal calculi, jaundice, discoloration of body fluids and aseptic meningitis.

HOW SUPPLIED

100 mg Tablets

Appearance: Dark brown coated, round standard cup tablet, debossed "611" on one side and plain on the other.

NDC: 70518-3986-00

NDC: 70518-3986-01

NDC: 70518-3986-02

PACKAGING: 30 in 1 BLISTER PACK

PACKAGING: 12 in 1 BOTTLE PLASTIC

PACKAGING: 6 in 1 BOTTLE PLASTIC

DISPENSE contents with a child-resistant closure (as required) and in a tight container as defined in the USP.

STORE at 20° to 25°C (68° to 77°F) with excursions permitted to 15° to 30°C (59° to 86°F) [See USP Controlled Room Temperature].

KEEP THIS AND ALL MEDICATION OUT OF THE REACH OF CHILDREN.

Repackaged and Distributed By:

Remedy Repack, Inc.

625 Kolter Dr. Suite #4 Indiana, PA 1-724-465-8762

Repackaged and Distributed By:

Remedy Repack, Inc.

625 Kolter Dr. Suite #4 Indiana, PA 1-724-465-8762

PACKAGE LABEL

DRUG: Phenazopyridine Hydrochloride

GENERIC: Phenazopyridine Hydrochloride

DOSAGE: TABLET

ADMINSTRATION: ORAL

NDC: 70518-3986-0

NDC: 70518-3986-1

NDC: 70518-3986-2

COLOR: brown

SHAPE: ROUND

SCORE: No score

SIZE: 7 mm

IMPRINT: 611

PACKAGING: 30 in 1 BLISTER PACK

PACKAGING: 12 in 1 BOTTLE PLASTIC

PACKAGING: 6 in 1 BOTTLE PLASTIC

ACTIVE INGREDIENT(S):

- PHENAZOPYRIDINE HYDROCHLORIDE 100mg in 1

INACTIVE INGREDIENT(S):

- STARCH, CORN
- CROSCARMELLOSE SODIUM
- D&C YELLOW NO. 10
- FD&C RED NO. 40
- FD&C BLUE NO. 1
- FD&C YELLOW NO. 6
- MICROCRYSTALLINE CELLULOSE
- MAGNESIUM STEARATE
- POVIDONE, UNSPECIFIED
- POLYVINYL ALCOHOL, UNSPECIFIED
- POLYETHYLENE GLYCOL, UNSPECIFIED
- SILICON DIOXIDE
- TALC
- TITANIUM DIOXIDE